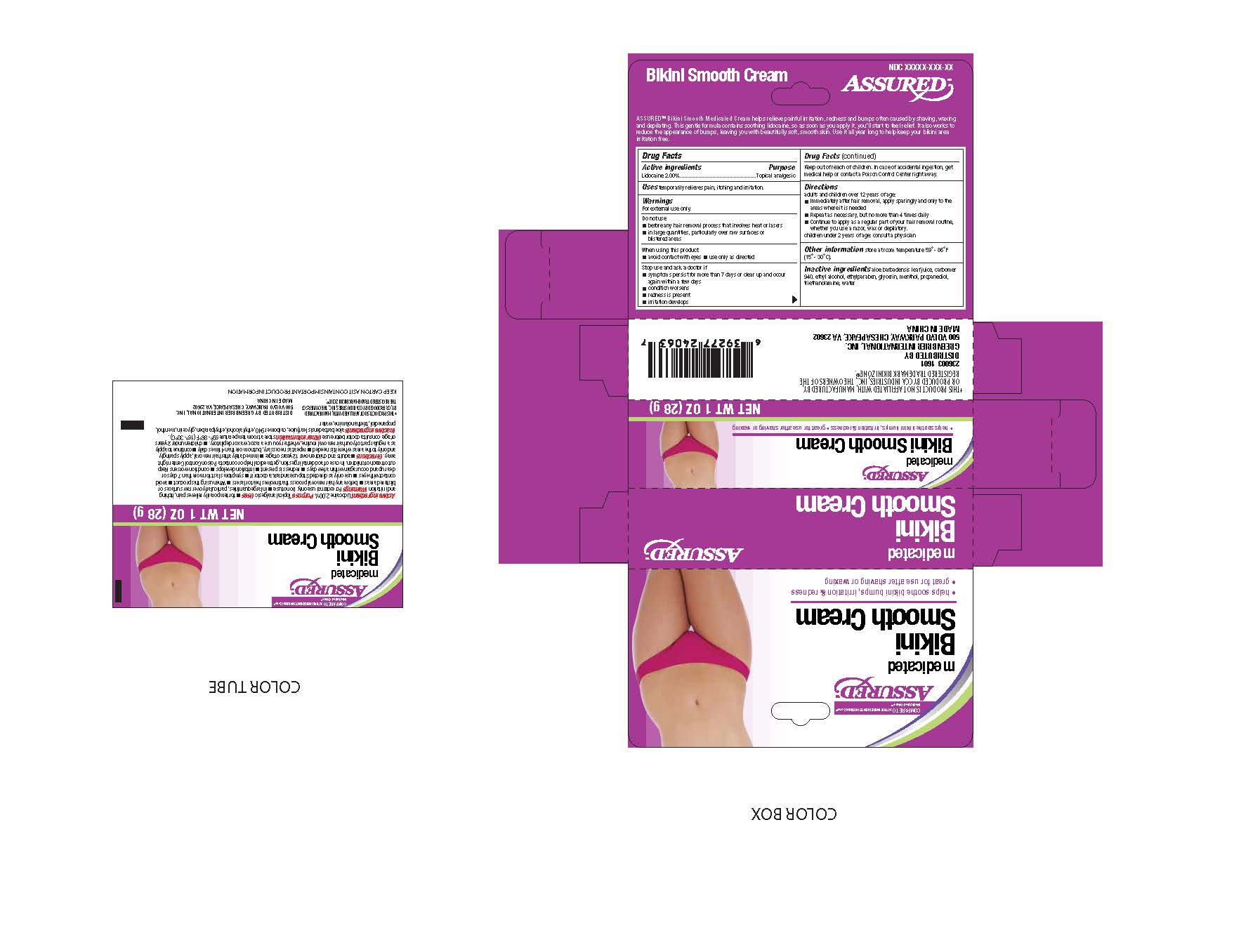 DRUG LABEL: 
                  Assured
                
                  

NDC: 55621-011 | Form: CREAM
Manufacturer: Zhejiang Jingwei Pharmaceutical Co., Ltd.
Category: otc | Type: HUMAN OTC DRUG LABEL
Date: 20231025

ACTIVE INGREDIENTS: LIDOCAINE 2 g/100 g
INACTIVE INGREDIENTS: CARBOMER HOMOPOLYMER TYPE C (ALLYL PENTAERYTHRITOL CROSSLINKED); ALCOHOL; ETHYLPARABEN; TROLAMINE; GLYCERIN; MENTHOL, UNSPECIFIED FORM; MALONDIALDEHYDE; ALOE VERA LEAF; WATER

Drug Facts

Active Ingredients

Lidocaine 2.00 %

Purpose

Topical analgesic

INDICATIONS AND USAGE

temporarily relieves pain, itching and irritation. Uses

Warnings

. For external use only

Do not use

-before any hair removal process that involves heat or lasers

-in large quantities, particularly over raw surfaces or

blistered areas

When using this product

-avoid contact with eyes -use only as directed

Stop use and ask a doctor if

-symptoms persist for more than 7 days or clear up and occur

again within a few days

-condition worsens

-redness is present

-irritation develops

KEEP OUT OF REACH OF CHILDREN

. In case of accidental ingestion, get Keep out of reach of children

medical help or contact a Poison Control Center right away.

Directions

adults and children over 12 years of age:

-immediately after hair removal, apply sparingly and only to the

areas where it is needed

-Repeat as necessary, but no more than 4 times daily

-Continue to apply as a regular part of your hair removal routine,

whether you use a razor, wax or depilatory

STORAGE AND HANDLING

store at room temperature 59 - 86 F Other information

(15 - 30 C)

aloe barbadensis leaf juice, carbomer Inactive Ingredients

940, ethyl alcohol, ethylparaben, glycerin, menthol, propanediol,

triethanolamine, water